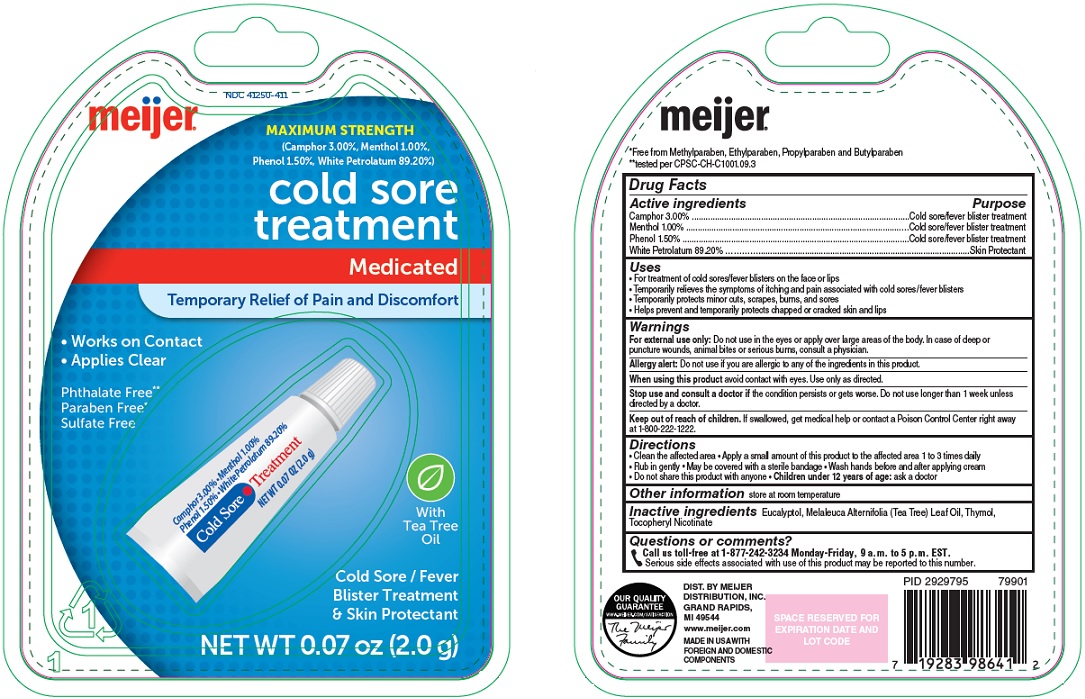 DRUG LABEL: Maximum Strength Cold Sore Treatment
NDC: 41250-411 | Form: GEL
Manufacturer: Meijer Distribution Inc
Category: otc | Type: HUMAN OTC DRUG LABEL
Date: 20241127

ACTIVE INGREDIENTS: CAMPHOR (SYNTHETIC) 30 mg/1 g; MENTHOL, UNSPECIFIED FORM 10 mg/1 g; PHENOL 15 mg/1 g; PETROLATUM 892 mg/1 g
INACTIVE INGREDIENTS: EUCALYPTOL; MELALEUCA ALTERNIFOLIA LEAF; THYMOL; TOCOPHERYL NICOTINATE

Maximum Strength Cold Sore Treatment - Meijer

Active ingredients

Camphor 3.00%

Menthol 1.00%

Phenol 1.50%

White Petrolatum 89.20%

Purpose

Cold sore/fever blister treatment

Skin Protectant

Uses

- For treatment of cold sores/fever blisters on the face or lips
- Temporarily relieves the symptoms of itching and pain associated with cold sores/fever blisters
- Temporarily protects minor cuts, scrapes, burns, and sores
- Helps prevent and temporarily protects chapped or cracked skin and lips

Warnings

For external use only: Do not use in the eyes or apply over large areas of the body. In case of deep or puncture wounds, animal bites or serious burns, consult a physician.

Allery alert: Do not use if you are allergic to any of the ingredients in this product.

When using this product

avoid contact with eyes. Use only as directed.

Stop use and consult a doctor if

the condition persists or gets worse. Do not use longer than 1 week unless directed by a doctor.

Keep out of reach of children.

If swallowed, get medical help or contact a Poison Control Center right away at 1-800-222-1222.

Directions

- Clean the affected area
- Apply a small amount of this product to the affected area 1 to 3 times daily
- Rub in gently
- May be covered with a sterile bandage
- Wash hands before and after applying cream
- Do not share this product with anyone
- Children under 12 years of age: ask a doctor

Other information

store at room temperature

Inactive ingredients

Eucalyptol, Melaleuca Alternifolia (Tea Tree) Leaf Oil, Thymol, Tocopheryl Nicotinate

Questions or comments?

Call us toll-free at 1-877-242-3234 Monday-Friday, 9 a.m. to 5 p.m. EST.

Serious side effects associated with use of this product may be reported to this number.

Principal Display Panel

MAXIMUM STRENGTH

(Camphor 3.00%, Menthol 1.00%, Phenol 1.5%, White Petrolatum 89.20%)

cold sore treatment

Medicated

Temporary Relief of Pain and Discomfort

Works on Contact

Applies Clear

Phthalate Free

Paraben Free

Sulfate Free

With Tea Tree Oil

Cold Sore / Fever Blister Treatment & Skin Protectant

NET WT 0.07 oz (2.0 g)